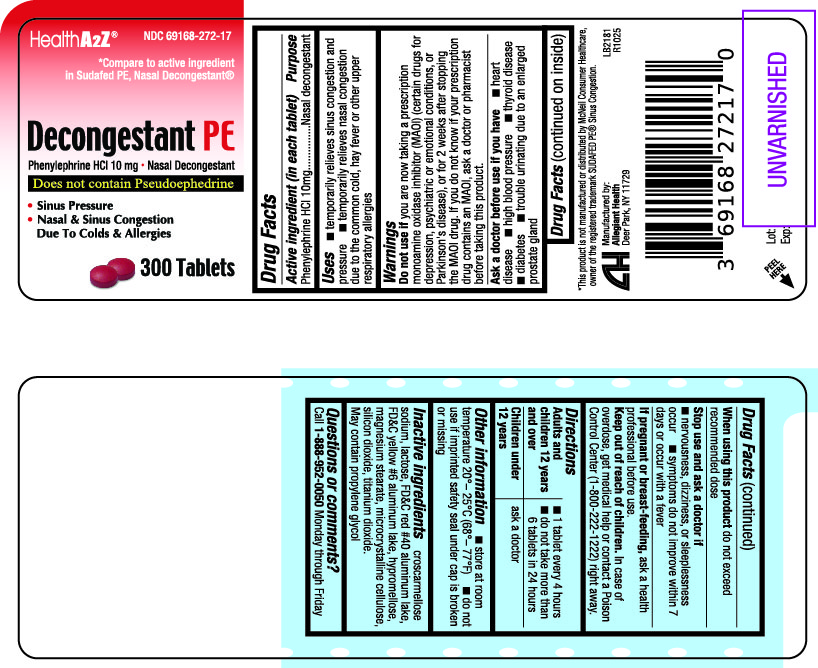 DRUG LABEL: Nasal Decongestant PE
NDC: 69168-272 | Form: TABLET
Manufacturer: Allegiant Health
Category: otc | Type: HUMAN OTC DRUG LABEL
Date: 20181107

ACTIVE INGREDIENTS: PHENYLEPHRINE HYDROCHLORIDE 10 mg/1 1
INACTIVE INGREDIENTS: CROSCARMELLOSE SODIUM; FD&C RED NO. 40; FD&C YELLOW NO. 6; HYPROMELLOSES; LACTOSE, UNSPECIFIED FORM; MAGNESIUM STEARATE; CELLULOSE, MICROCRYSTALLINE; POLYETHYLENE GLYCOL, UNSPECIFIED; PROPYLENE GLYCOL; SILICON DIOXIDE; TITANIUM DIOXIDE

Drug Facts

Active ingredient

Phenylephrine HCl 10 mg

Purpose

Nasal Decongestant

Uses

temporarily relieves:

- nasal congestion due to the common cold, hay fever, or other upper respiratory allergies
- nasal congestion associated with sinusitis
- sinus congestion and pressure

Warnings

Do not use if you are now taking a prescription mono-amine oxidase inhibitor (MAOI) (certain drugs for depression, psychiatric or emotional conditions, or

Parkinson’s disease), or for 2 weeks after stopping the MAOI drug. If you do not know if your prescription drug contains an MAOI, ask a doctor or pharmacist before taking this product.

Ask a doctor before use if you have

- heart disease
- high blood pressure
- thyroid disease
- diabetes
- trouble urinating due to an enlarged prostate gland

When using this product

do not use more than directed

Stop use and ask a doctor if

- you get nervous, dizzy, or sleepless
- symptoms do not improve within 7 days or are accompanied by fever

Keep Out of Reach of Children

In case of accidentaloverdose, contact a Poison Control Center (1-800-222-1222) right away.

Directions

- Adults and children 12 years of age and older:
- 1 tablet every 4 to 6 hours.
- Do not take more than 6 tablets in 24 hours
- Children under 12 years of age: ask a doctor

Inactive Ingredients

croscarmellose sodium, FD&C red #40 aluminum lake, FD&C yellow #6 aluminum lake, hypromellose, lactose, magnesium stearate, microcrystalline cellulose, polyethylene glycol, silicon dioxide, titanium dioxide

If pregnant or breast-feeding, ask a health professionalbefore use.

Principal Display Panel

Decongestant PE